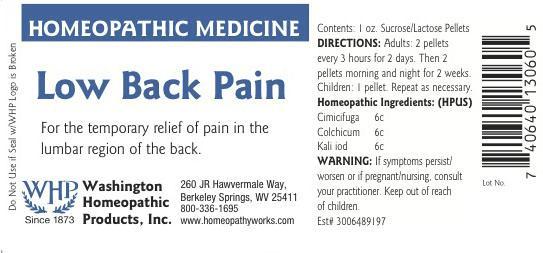 DRUG LABEL: Low Back Pain
NDC: 68428-022 | Form: PELLET
Manufacturer: Washington Homeopathic Products
Category: homeopathic | Type: HUMAN OTC DRUG LABEL
Date: 20191223

ACTIVE INGREDIENTS: BLACK COHOSH 6 [hp_C]/28 g; COLCHICUM AUTUMNALE BULB 6 [hp_C]/28 g; POTASSIUM IODIDE 6 [hp_C]/28 g
INACTIVE INGREDIENTS: SUCROSE; LACTOSE

DRUG FACTS

ACTIVE INGREDIENTS

CIMICIFUGA 6C

COLCHICUM 6C

KALI IOD 6C

USES

To relieve the symptoms of for the temporary relief of pain in the lumbar region of the back.

KEEP OUT OF REACH OF CHILDREN

Keep this and all medicines out of reach of children.

INDICATIONS

CIMICIFUGA Back pains

COLCHICUM Bloating

KALI IOD Swollen glands

STOP USE AND ASK DOCTOR

If symptoms persist/worsen or if pregnant/nursing, stop use and consult your practitioner.

DIRECTIONS

Adults 2 pellets every 3 hours for 2 days. Then 2 pellets morning and night for 2 weeks.

Children: 1 pellet. Repeat as necessary.

INACTIVE INGREDIENTS

Sucrose/Lactose

PRINCIPAL DISPLAY PANEL

Enter section text here